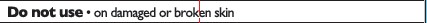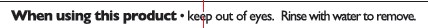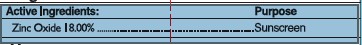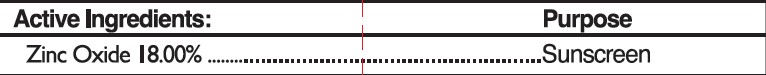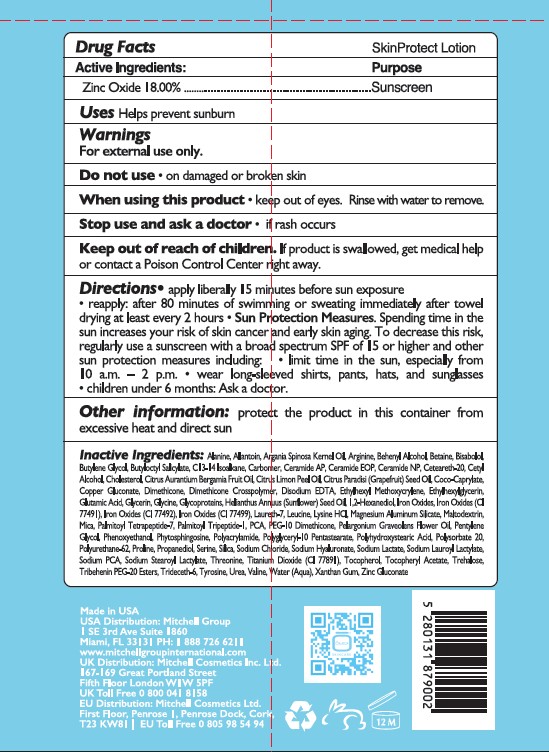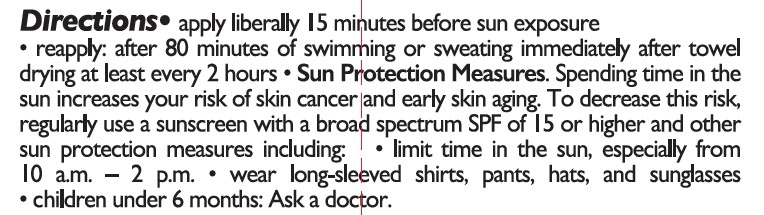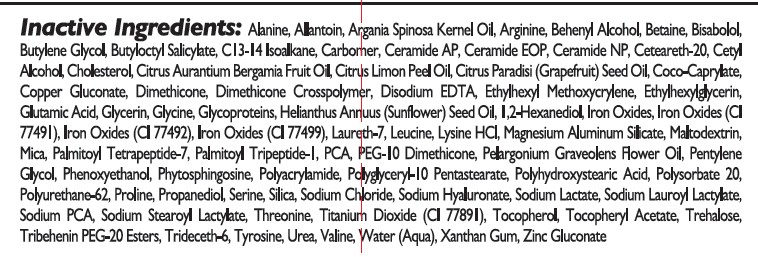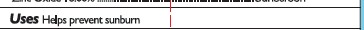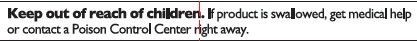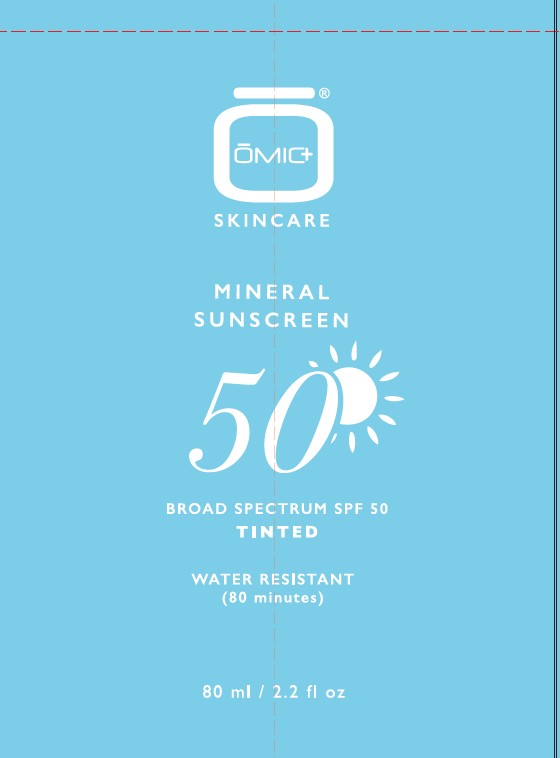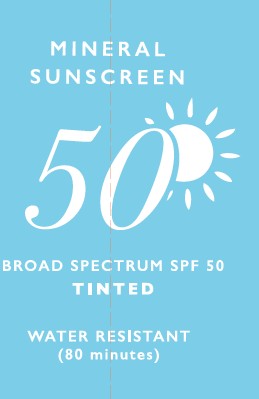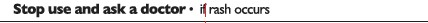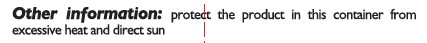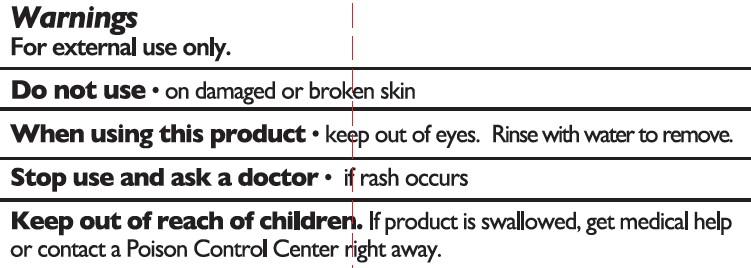 DRUG LABEL: OMIC MINERAL SUNSCREEN
NDC: 79009-902 | Form: LOTION
Manufacturer: Mitchell Cosmetics, Inc
Category: otc | Type: HUMAN OTC DRUG LABEL
Date: 20260225

ACTIVE INGREDIENTS: ZINC OXIDE 0.18 g/1 g
INACTIVE INGREDIENTS: CETEARETH-20; 1,2-HEXANEDIOL; BUTYLENE GLYCOL; BETAINE; COPPER GLUCONATE; TYROSINE; VALINE; C13-14 ISOPARAFFIN; CHOLESTEROL; LYSINE HCL; MALTODEXTRIN; PHYTOSPHINGOSINE; XANTHAN GUM; POLYSORBATE 20; SILICON DIOXIDE; BEHENYL ALCOHOL; LEUCINE; SODIUM LACTATE; ARGININE; PCA; CETYL ALCOHOL; SODIUM PCA; PROPANEDIOL; SODIUM CHLORIDE; PENTYLENE GLYCOL; BUTYLOCTYL SALICYLATE; ALANINE; CI 77491; EDETATE DISODIUM; ALLANTOIN; BISABOLOL; POLYGLYCERYL-10 PENTASTEARATE; CI 77492; POLYACRYLAMIDE (10000 MW); BERGAMOT OIL; POLYURETHANE-62; CERAMIDE 9; CERAMIDE NP; CITRUS PARADISI (GRAPEFRUIT) SEED OIL; PEG-10 DIMETHICONE (600 CST); PLATELET GLYCOPROTEIN VI; MAGNESIUM ALUMINUM SILICATE; ARGANIA SPINOSA KERNEL OIL; GLYCINE; PALMITOYL TRIPEPTIDE-1; SODIUM LAUROYL LACTYLATE; LAURETH-7; CERAMIDE AP; COCO-CAPRYLATE; DIMETHICONE; DIMETHICONE CROSSPOLYMER (450000 MPA.S AT 12% IN CYCLOPENTASILOXANE); TITANIUM DIOXIDE; .ALPHA.-TOCOPHEROL ACETATE; UREA; ZINC GLUCONATE; PALMITOYL TETRAPEPTIDE-7; CI 77499; PROLINE; SODIUM HYALURONATE; SODIUM STEAROYL LACTYLATE; TOCOPHEROL; TRIDECETH-6; PELARGONIUM GRAVEOLENS FLOWER OIL; ETHYLHEXYLGLYCERIN; GLUTAMIC ACID; TREHALOSE; POLYHYDROXYSTEARIC ACID (2300 MW); SERINE; ETHYLHEXYL METHOXYCRYLENE; AQUA; THREONINE; LEMON OIL, COLD PRESSED; MICA; TRIBEHENIN PEG-20 ESTERS; CARBOMER; HELIANTHUS ANNUUS (SUNFLOWER) SEED OIL; PHENOXYETHANOL; GLYCERIN

OMIC MINERAL SUNSCREEN